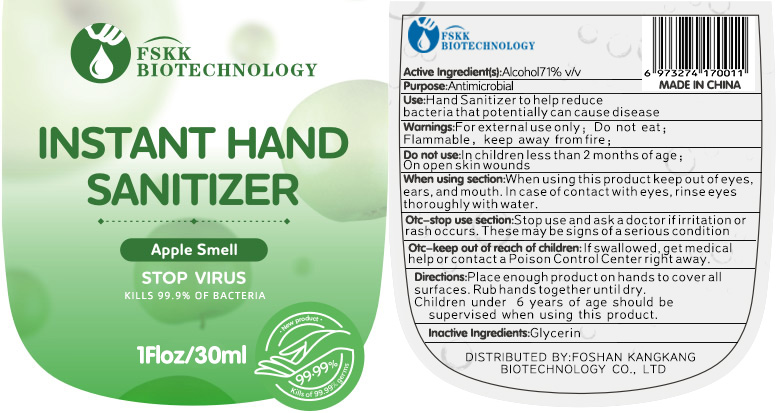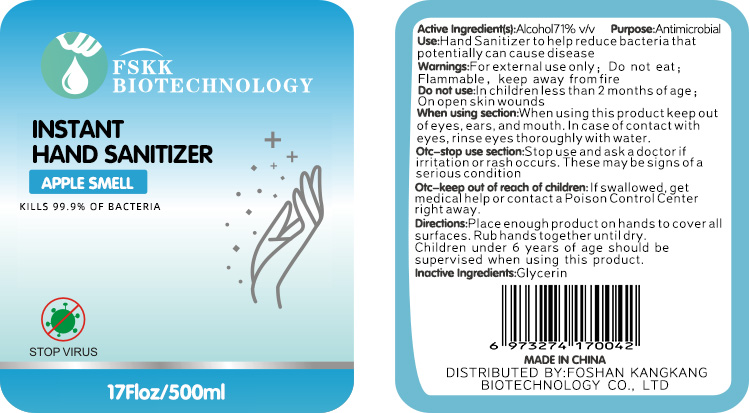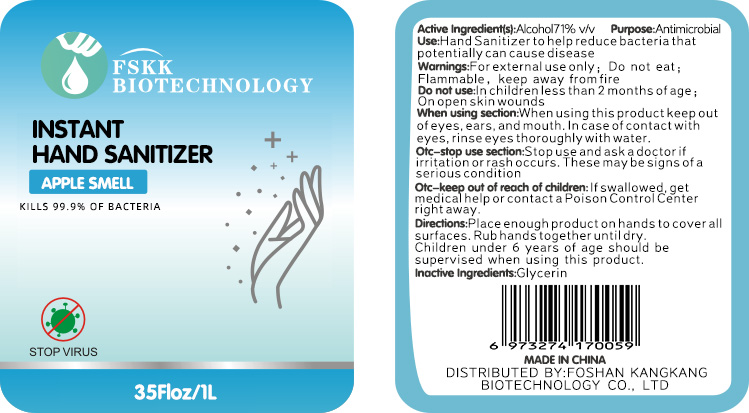 DRUG LABEL: INSTANT HAND SANITIZER
NDC: 78413-001 | Form: GEL
Manufacturer: FOSHAN KANGKANG BIOTECHNOLOGY?CO.,LTD
Category: otc | Type: HUMAN OTC DRUG LABEL
Date: 20200609

ACTIVE INGREDIENTS: ALCOHOL 71 mL/100 mL
INACTIVE INGREDIENTS: GLYCERIN

INSTANT HAND SANITIZER

Active Ingredient(s)

Alcohol 71% v/v

Purpose

Antimicrobial

Use

Hand Sanitizer to help reduce bacteria that potentially can cause disease

Warnings

For external use only; Do not eat ;Flammable,keep away from fire

Do not use

In children less than 2 months of age ; On open skin wounds.

When using this product

keep out of eyes, ears, and mouth. In case of contact with eyes, rinse eyes thoroughly with water.

Stop use and ask a doctor

if irritation or rash occurs. These may be signs of a serious condition.

keep out of reach of children

If swallowed, get medical help or contact a Poison Control Center right away.

Directions

Place enough product on hands to cover all surfaces. Rub hands together until dry.

Children under 6 years of age should be supervised when using this product.

Inactive Ingredients

Glycerin